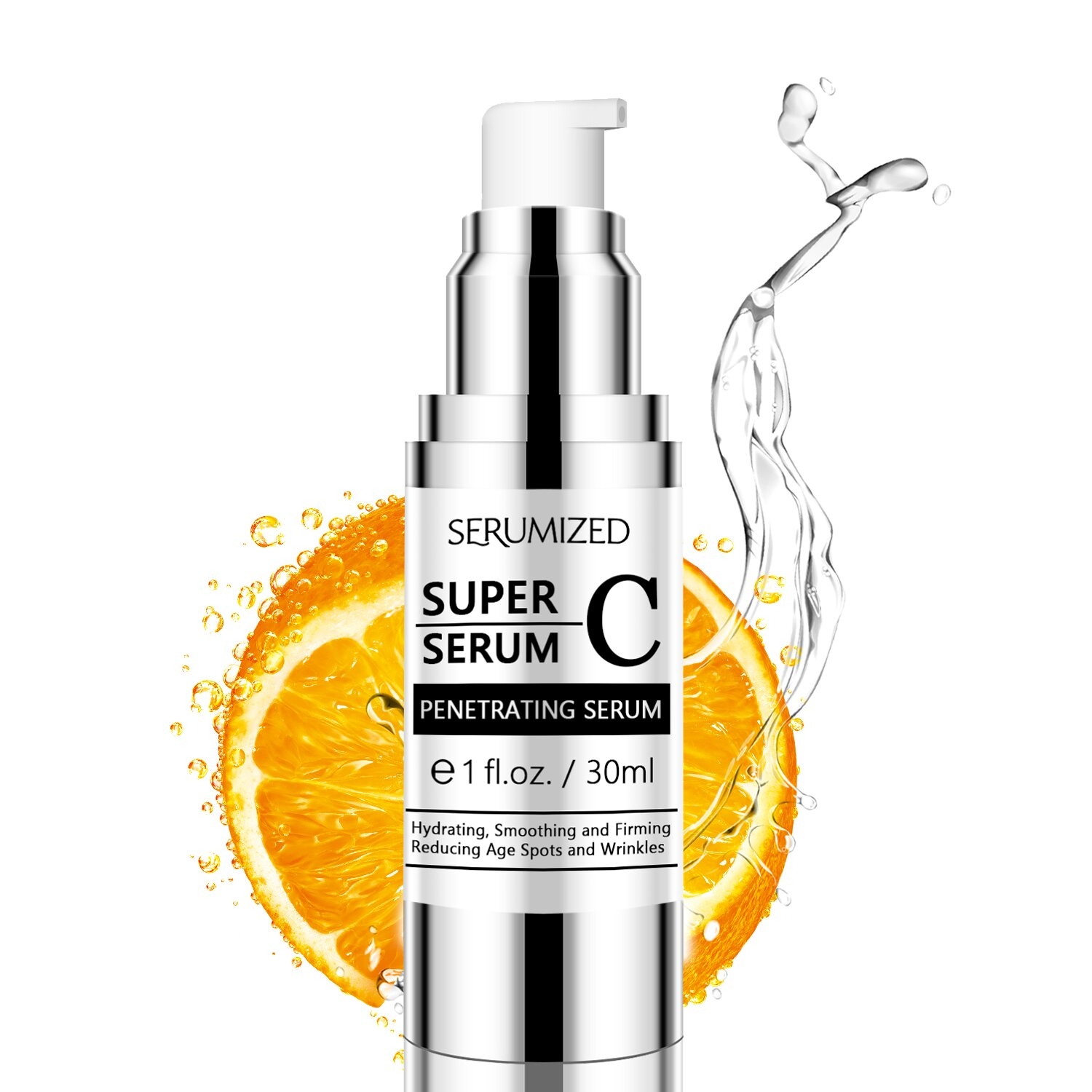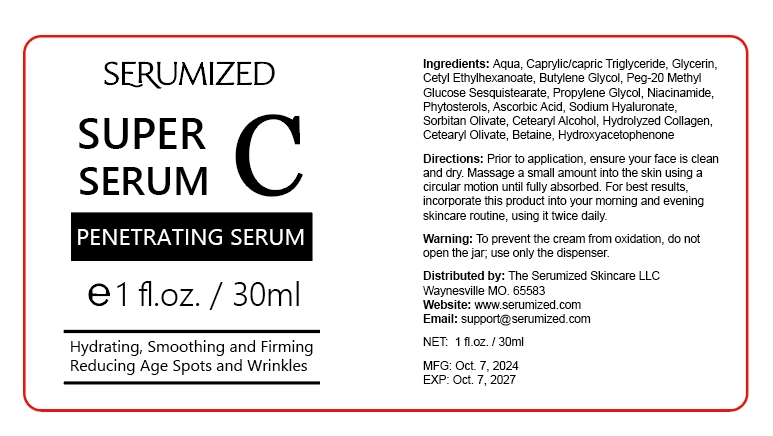 DRUG LABEL: SUPER C SERUM
NDC: 84025-292 | Form: CREAM
Manufacturer: Guangzhou Yanxi Biotechnology Co., Ltd
Category: otc | Type: HUMAN OTC DRUG LABEL
Date: 20241220

ACTIVE INGREDIENTS: GLYCERIN 5 mg/30 mL; CAPRYLIC/CAPRIC TRIGLYCERIDE 3 mg/30 mL
INACTIVE INGREDIENTS: WATER

DOSAGE AND ADMINISTRATION

Massage a small amount into the skin using acircular motion until fully absorbed.

WARNINGS

Keep out of children

INACTIVE INGREDIENT

Aqua

INDICATIONS AND USAGE

For daily skin care

Keep out of children

PURPOSE

Hydrating and smoothing skin